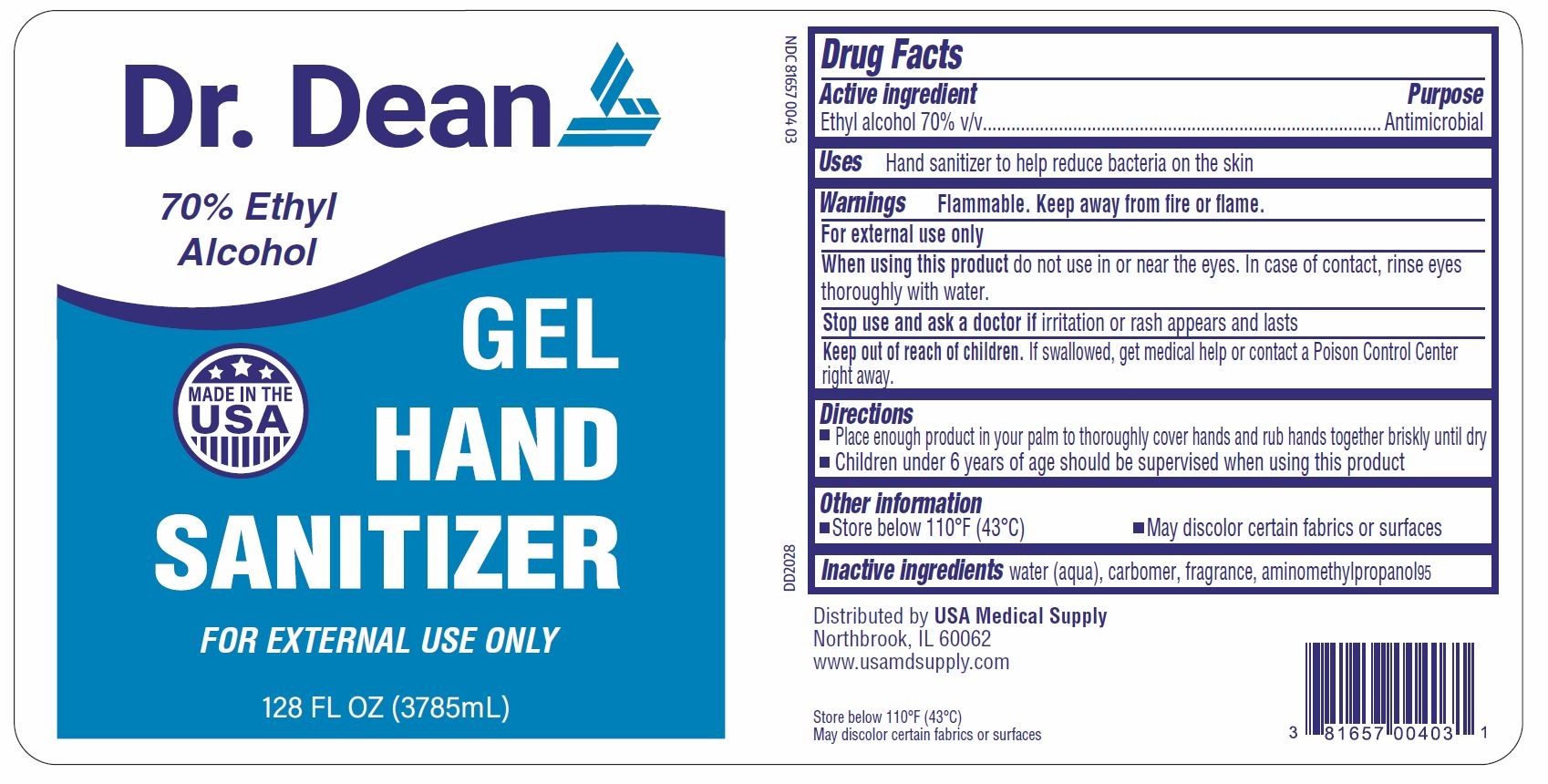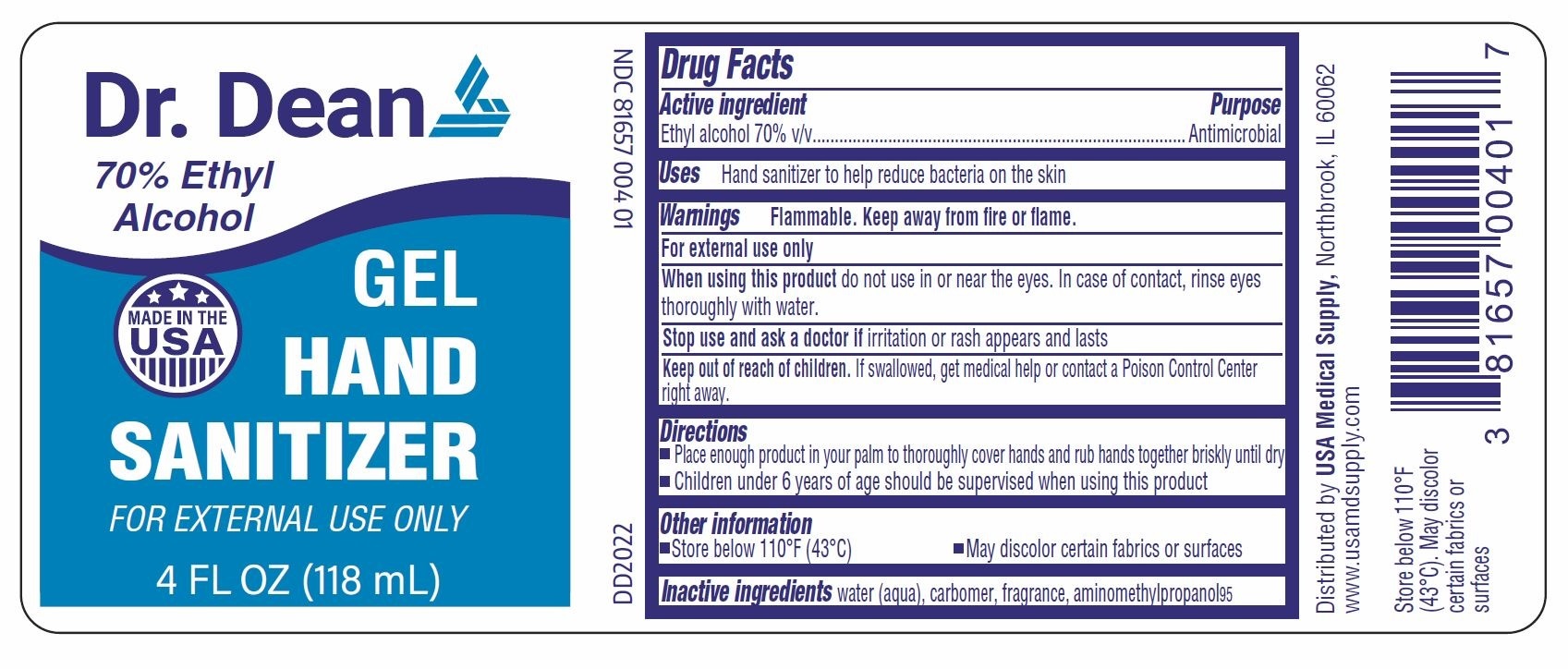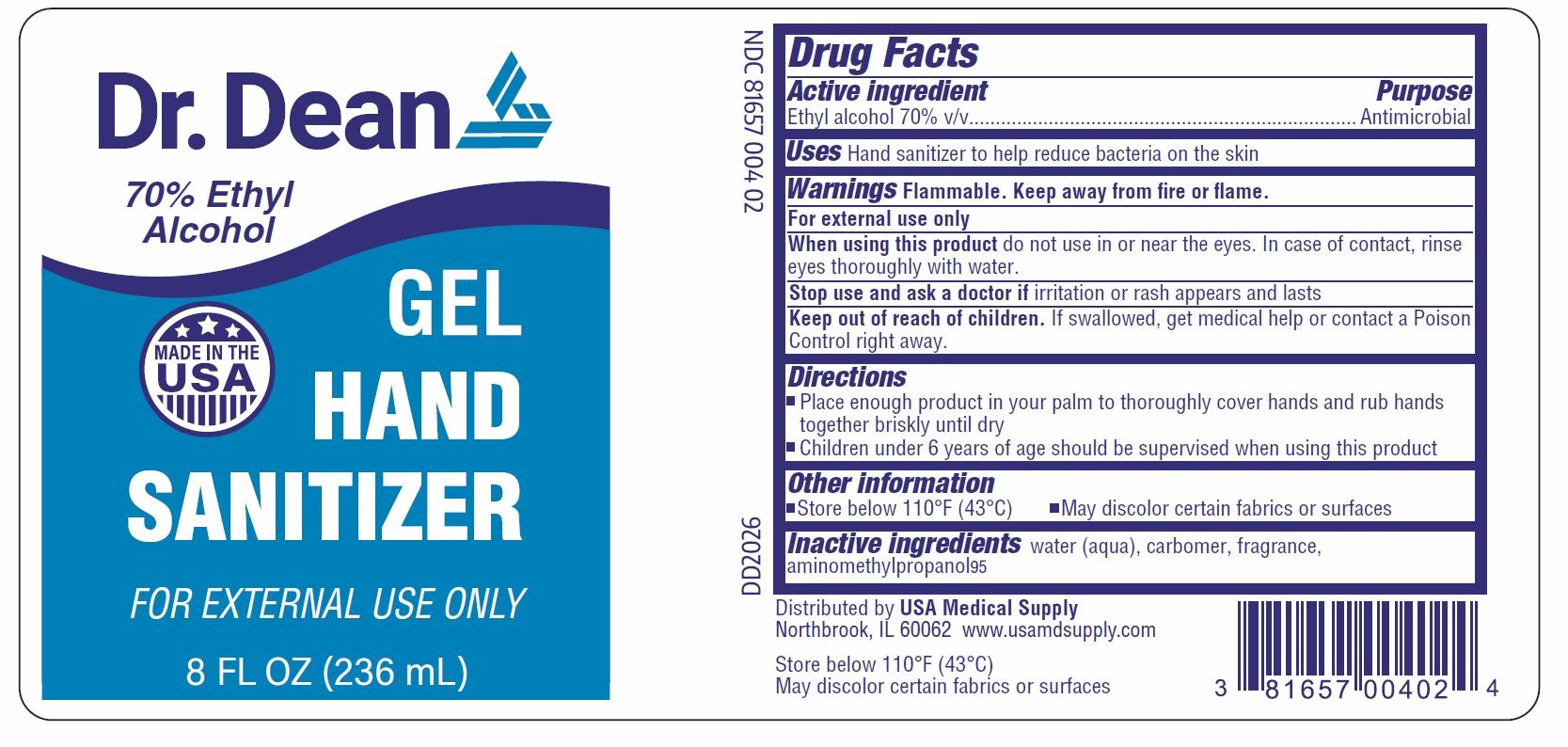 DRUG LABEL: Hand Sanitizer Gel
NDC: 81657-004 | Form: GEL
Manufacturer: USA Medical Supply LLC
Category: otc | Type: HUMAN OTC DRUG LABEL
Date: 20210618

ACTIVE INGREDIENTS: ALCOHOL 0.7 mL/1 mL
INACTIVE INGREDIENTS: AMINOMETHYLPROPANOL; CARBOMER 940; WATER

Drug Facts

Active ingredient

Ethyl alcohol 70% v/v

Purpose

Antimicrobial

Use

Hand sanitizer to help reduce bacteria on the skin

Warnings

Flammable. Keep away from fire or flame.

For external use only

When using this product

do not use in or near the eyes. In case of contact, rinse eyes thoroughly with water.

Stop use and ask a doctor if

irritation or rash appears and lasts

Keep out of reach of children.

If swallowed, get medical help or contact a Poison Control right away.

Directions

- Place enough product in your palm to thoroughly cover hands and rub hands together briskly until dry
- Children under 6 years of age should be supervised when using this product

Other information

- Store below 110°F (43°C)
- May discolor certain fabrics or surfaces

Inactive ingredients

water (aqua), carbomer, fragrance, propanediol 2-amino methyl-1 propanol solution

Package/Label Principal Display Panel

DR. DEAN

70% Ethyl Alcohol

GEL HAND SANITIZER

MADE IN THE USA

FOR EXTERNAL USE ONLY

4 fl oz (118 mL)

NDC 81657-004-01

Drug Facts

Distributed by USA Medical Supply

Northbrook, IL 60062

www.usamdsupply.com

Store below 110°F (43°C)

May discolor certain fabrics or surfaces

DR. DEAN

70% Ethyl Alcohol

GEL HAND SANITIZER

MADE IN THE USA

FOR EXTERNAL USE ONLY

8 fl oz (236 mL)

NDC 81657-004-02

Drug Facts

Distributed by USA Medical Supply

Northbrook, IL 60062

www.usamdsupply.com

Store below 110°F (43°C)

May discolor certain fabrics or surfaces

DR. DEAN

70% Ethyl Alcohol

GEL HAND SANITIZER

MADE IN THE USA

FOR EXTERNAL USE ONLY

128 fl oz (3785 mL)

NDC 81657-004-03

Drug Facts

Distributed by USA Medical Supply

Northbrook, IL 60062

www.usamdsupply.com

Store below 110°F (43°C)

May discolor certain fabrics or surfaces